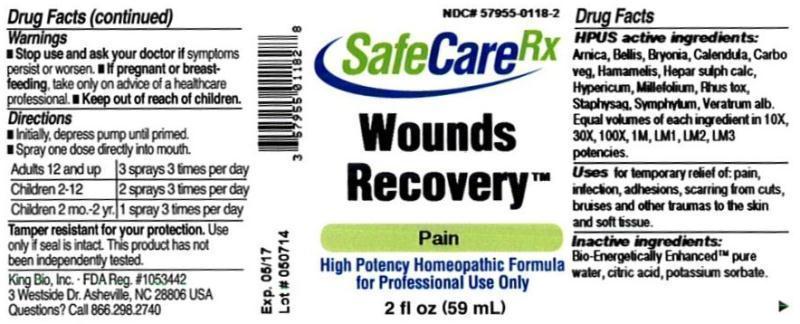 DRUG LABEL: Wounds Recovery
NDC: 57955-0118 | Form: LIQUID
Manufacturer: King Bio Inc.
Category: homeopathic | Type: HUMAN OTC DRUG LABEL
Date: 20140528

ACTIVE INGREDIENTS: ARNICA MONTANA 10 [hp_X]/59 mL; BELLIS PERENNIS 10 [hp_X]/59 mL; BRYONIA ALBA ROOT 10 [hp_X]/59 mL; CALENDULA OFFICINALIS FLOWERING TOP 10 [hp_X]/59 mL; ACTIVATED CHARCOAL 10 [hp_X]/59 mL; HAMAMELIS VIRGINIANA ROOT BARK/STEM BARK 10 [hp_X]/59 mL; CALCIUM SULFIDE 10 [hp_X]/59 mL; HYPERICUM PERFORATUM 10 [hp_X]/59 mL; ACHILLEA MILLEFOLIUM 10 [hp_X]/59 mL; TOXICODENDRON PUBESCENS LEAF 10 [hp_X]/59 mL; DELPHINIUM STAPHISAGRIA SEED 10 [hp_X]/59 mL; COMFREY ROOT 10 [hp_X]/59 mL; VERATRUM ALBUM ROOT 10 [hp_X]/59 mL
INACTIVE INGREDIENTS: WATER; CITRIC ACID MONOHYDRATE; POTASSIUM SORBATE

Wounds Recovery™

ACTIVE INGREDIENT

Drug Facts__________________________________________________________________________________________________________

HPUS active ingredients: Arnica montana, Bellis perennis, Bryonia, Calendula officinalis, Carbo vegetabilis, Hamamelis virginiana, Hepar sulphuris calcareum, Hypericum perforatum, Millefolium, Rhus toxicodendron, Staphysagria, Symphytum officinale, Veratrum album. Equal volumes of each ingredient in 10X, 30X, 100X, 1M, LM1, LM2, LM3 potencies.

INDICATIONS AND USAGE

Uses for temporary relief of: pain, infection, adhesions, scarring from cuts, bruises and other traumas to the skin and soft tissue.

INACTIVE INGREDIENT

Inactive Ingredients: Bio-Energetically Enhanced™ pure water, citric acid and potassium sorbate.

Warnings

- Stop use and ask your doctor if symptoms persist or worsen.
- If pregnant or breast-feeding, take only on advice of a healthcare professional.

- Keep out of reach of children.

Directions

- Initially, depress pump until primed.
- Spray one dose directly into mouth.
- Adults: 3 sprays 3 times per day.
- Children 2-12 years: 2 sprays 3 times per day.
- Children 2 mo-2 yr. 1 spray 3 times per day.

OTHER SAFETY INFORMATION

Tamper resistant for your protection. Use only if safety seal is intact. This product has not been independently tested.

PURPOSE

Uses for temporary relief of:

- pain
- infection
- adhesions
- scarring from cuts
- bruises and other traumas to the skin and soft tissue